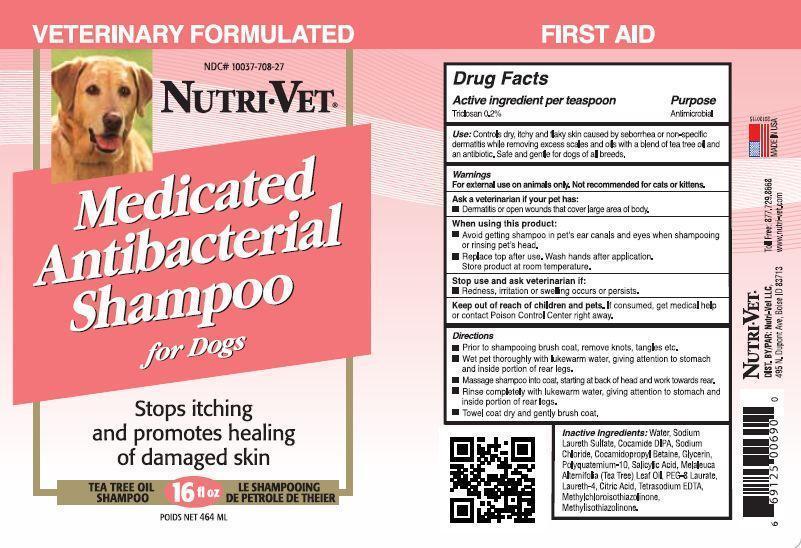 DRUG LABEL: Nutri Vet 
NDC: 10037-708 | Form: SHAMPOO
Manufacturer: Nutri-Vet LLC
Category: animal | Type: OTC ANIMAL DRUG LABEL
Date: 20130429

ACTIVE INGREDIENTS: Triclosan 0.2 g/100 mL
INACTIVE INGREDIENTS: Water; Sodium Laureth Sulfate; COCO DIISOPROPANOLAMIDE; Sodium Chloride; Cocamidopropyl Betaine; GLYCERIN; POLYQUATERNIUM-10 (400 CPS AT 2%); SALICYLIC ACID; Tea Tree Oil; PEG-8 LAURATE; LAURETH-4; Citric Acid Monohydrate; Edetate Sodium; Methylchloroisothiazolinone; Methylisothiazolinone

Drug Facts

Active ingredient per teaspoon

Triclosan 0.2%

Purpose

Antimicrobial

INDICATIONS AND USAGE

Use: Controls dry,itchy and flaky skin caused by seborrhea or non-specific dermatitis while removing excess scales and oils with a blend of tea tree oil and an antibiotic. Safe and gentle for dogs of all breeds.

Warnings

For external use on animals only. Not recommended for cats or kittens.

Ask a veterinarian if your pet has:

Dermatitis or open wounds that cover large area of body.

When using this product:

Avoid getting shampoo in pet's ear canals and eyes when shampooing

or rinsing pet's head.

Replace top after use.Wash hands after application.

Store product at room temperature.

Stop use and ask veterinarian if:

redness,irritation or swelling occurs or persists.

Keep out of reach of children and pets. If consumed, get medical help

or contact Poison Control Center right away.

Directions

Prior to shampooing brush coat, remove knots, tangles, etc.

Wet pet thoroughly with lukewarm water, giving attention to stomach

and inside portion of rear legs.

Massage shampoo into coat,starting at back of head and work towards rear.

Rinse completely with lukewarm water, giving attention to stomach and

inside portion of rear legs.

Towel coat dry and gently brush coat.

INACTIVE INGREDIENT

Inactive Ingredients Water, Sodium Laureth Sulfate, Cocamide DEA, Sodium Chloride, Cocamidopropyl Betaine, Polyquaternium-10, Salicylic acid, Melaleuca Alternifolia (Tea Tree) Leaf Oil, Citric Acid, Tetrasodium EDTA, Methychloroisothiazolinine, Methylisothiazolinone